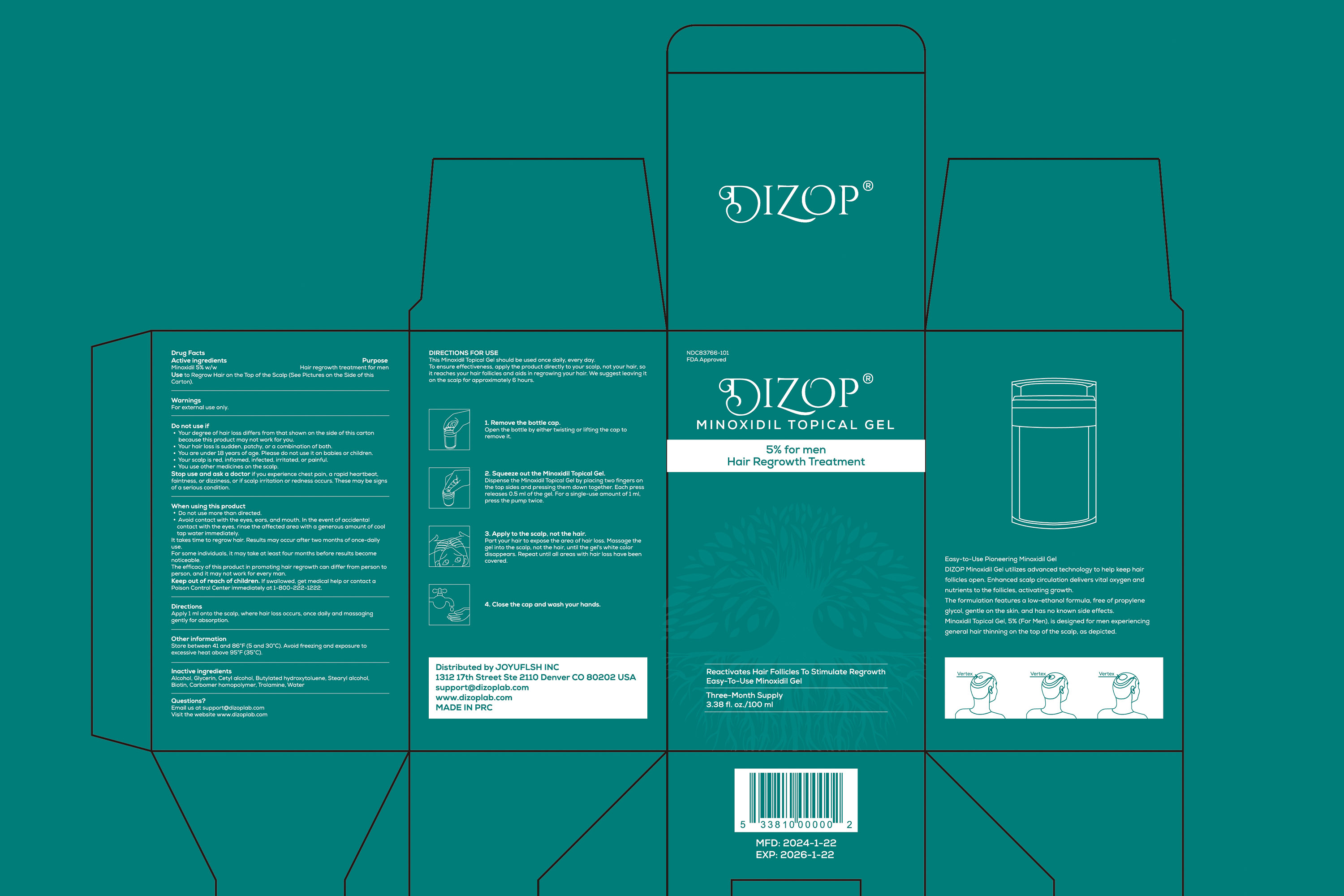 DRUG LABEL: Dizop Minoxidil Topical Gel
NDC: 83766-101 | Form: GEL
Manufacturer: Shenzhen Joyuflsh Technology Co.,Ltd.
Category: otc | Type: HUMAN OTC DRUG LABEL
Date: 20240423

ACTIVE INGREDIENTS: MINOXIDIL 5 g/100 mL
INACTIVE INGREDIENTS: CARBOMER HOMOPOLYMER, UNSPECIFIED TYPE; POLYSORBATE 80; STEARIC ACID; SORBITAN MONOOLEATE; GLYCERIN; OLEIC ACID; WATER; BIOTIN

Dizop Minoxidil Topical Gel

Dizop Minoxidil Topical Gel

ACTIVE INGREDIENT

Minoxidil 5%

PURPOSE

Reactivates Hair Follicles To Stimulate RegrowthEasy-To-Use Minoxidil Gel

Minoxidil Topical Gel, 5% (For Men), is designed for men experiencing general hair
thinning on the top of the scalp, as depicted.

INDICATIONS AND USAGE

Hair regrowth treatment for men.
Use to Regrow Hair on the Top of the Scalp (See Pictures on the Side of this Carton).

WARNINGS

For external use only

DO NOT USE

Your degree of hair loss differs from that shown on the side of this carton because this product may not work for you.
Your hair loss is sudden, patchy, or a combination of both.
You are under 18 years of age. Please do not use it on babies or children.
Your scalp is red, inflamed, infected, irritated, or painful.
You use other medicines on the scalp.

Do not use more than directed.
Avoid contact with the eyes, ears, and mouth. In the event of accidental contact withthe eyes, rinse the affected area with a generous amount of cool tap waterimmediately.
lt takes time to regrow hair. Results may occur after two months of once-daily useFor some individuals, it may take at least four months before results becomenoticeable.
The efficacy of this product in promoting hair regrowth can differ from person to person, and it may not work for every man.

Stop use and ask a doctor if you experience chest pain, a rapid heartbeat,faintness, or dizziness, or if scalp irritation or redness occurs. These may be signs of a serious condition

Keep out of reach of children. lf swallowed, get medical help or contact a Poison Control Center immediately at 1-800-222-1222

DOSAGE AND ADMINISTRATION

Apply 1 ml onto the scalp, where hair loss occurs, once daily and massaging gently for absorption.

STORAGE AND HANDLING

Store between 41 and 86℉ (5 and 30 ℃). Avoid freezing and exposure to excessive heat above 95℉ (35°C)

INACTIVE INGREDIENT

STEARIC ACID
OLEIC ACID
POLYSORBATE 80
SORBITAN MONOOLEATE
CARBOMER HOMOPOLYMER
GLYCERIN
PURIFIED WATER